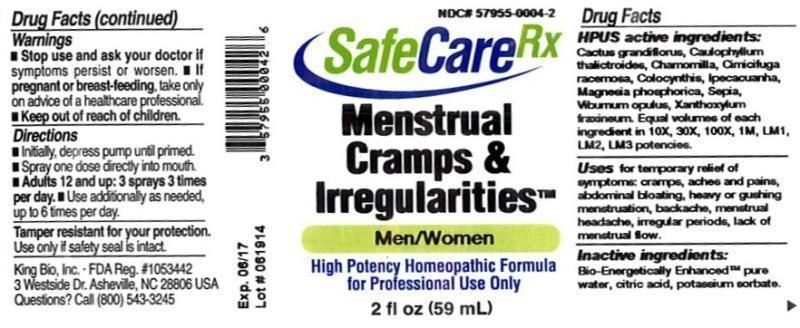 DRUG LABEL: Menstrual Cramps and Irregularities
NDC: 57955-0004 | Form: LIQUID
Manufacturer: King Bio Inc.
Category: homeopathic | Type: HUMAN OTC DRUG LABEL
Date: 20150223

ACTIVE INGREDIENTS: SELENICEREUS GRANDIFLORUS STEM 10 [hp_X]/59 mL; CAULOPHYLLUM THALICTROIDES ROOT 10 [hp_X]/59 mL; MATRICARIA RECUTITA 10 [hp_X]/59 mL; BLACK COHOSH 10 [hp_X]/59 mL; CITRULLUS COLOCYNTHIS FRUIT PULP 10 [hp_X]/59 mL; IPECAC 10 [hp_X]/59 mL; MAGNESIUM PHOSPHATE, DIBASIC TRIHYDRATE 10 [hp_X]/59 mL; SEPIA OFFICINALIS JUICE 10 [hp_X]/59 mL; VIBURNUM OPULUS BARK 10 [hp_X]/59 mL; ZANTHOXYLUM AMERICANUM BARK 10 [hp_X]/59 mL
INACTIVE INGREDIENTS: WATER; ANHYDROUS CITRIC ACID; POTASSIUM SORBATE

Menstrual Cramps and Irregularities™

ACTIVE INGREDIENT

Drug Facts__________________________________________________________________________________________________________

HPUS active ingredients: Cactus grandiflorus, Caulophyllum thalictroides, Chamomilla, Cimicifuga racemosa, Colocynthis, Ipecacuanha, Magnesia phosphorica, Sepia, Viburnum opulus, Xanthoxylum fraxineum. Equal volumes of each ingredient in 10X, 30X, 100X, 1M, LM1, LM2, LM3 potencies.

INDICATIONS AND USAGE

Uses for temporary relief of symptoms: cramps, aches and pains, Abdominal bloating, heavy or gushing menstruation, backache, menstrual headache, irregular periods, lack of menstrual flow.

Inactive Ingredients:

Bio-Energetically Enhanced™ pure water, citric acid and potassium sorbate.

Warnings

- Stop use and ask your doctor if symptoms persist or worsen.
- If pregnant or breast-feeding, take only on advice of a healthcare professional.

- Keep out of reach of children.

Directions

- Initially, depress pump until primed.
- Spray one dose directly into mouth.
- Adults 12 and up: 3 sprays 3 times per day
- Use additionally as needed up to 6 times per day.

OTHER SAFETY INFORMATION

Tamper resistant for your protection. Use only if safety seal is intact.

PURPOSE

Uses for temporary relief of symptoms:

- cramps
- aches and pains
- abdominal bloating
- heavy or gushing menstruation
- backache
- menstrual headache
- irregular periods
- lack of menstrual flow